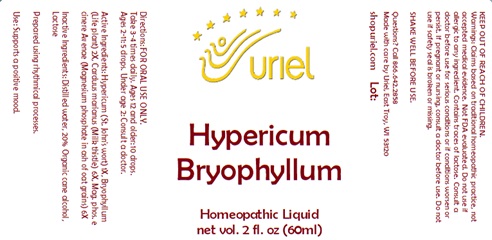 DRUG LABEL: Hypericum Bryophyllum
NDC: 48951-5060 | Form: LIQUID
Manufacturer: Uriel Pharmacy Inc.
Category: homeopathic | Type: HUMAN OTC DRUG LABEL
Date: 20241217

ACTIVE INGREDIENTS: ST. JOHN'S WORT 1 [hp_X]/1 mL; KALANCHOE DAIGREMONTIANA LEAF 2 [hp_X]/1 mL; MILK THISTLE 6 [hp_X]/1 mL; MAGNESIUM PHOSPHATE, TRIBASIC, PENTAHYDRATE 6 [hp_X]/1 mL
INACTIVE INGREDIENTS: WATER; ALCOHOL; LACTOSE

Hypericum Bryophyllum

INDICATIONS AND USAGE

Directions: FOR ORAL USE ONLY.

DOSAGE AND ADMINISTRATION

Take 3-4 times daily. Ages 12 and older: 10 drops. Ages 2-11: 5 drops. Under age 2: Consult a doctor.

ACTIVE INGREDIENT

Active Ingredients: Hypericum (St. John's wort) 1X, Bryophyllum (Life plant) 2X, Carduus marianus (Milk thistle) 6X, Mag. phos. e cinere Avenae (Magnesium phosphate in ash of oat grains) 6X

Inactive Ingredients: Distilled water, Organic cane alcohol, Lactose

Prepared using rhythmical processes.

PURPOSE

Use: Supports a positive mood.

KEEP OUT OF REACH OF CHILDREN.

WARNINGS

Warnings: Claims based on traditional homeopathic practice, not accepted medical evidence. Not FDA evaluated. Do not use if allergic to any ingredient. Contains traces of lactose. Consult a doctor before use for serious conditions or if conditions worsen or persist. If pregnant or nursing, consult a doctor before use. Do not use if safety seal is broken or missing.

QUESTIONS

Questions? Call 866.642.2858 Made with care by Uriel, East Troy, WI 53120 shopuriel.com Lot: